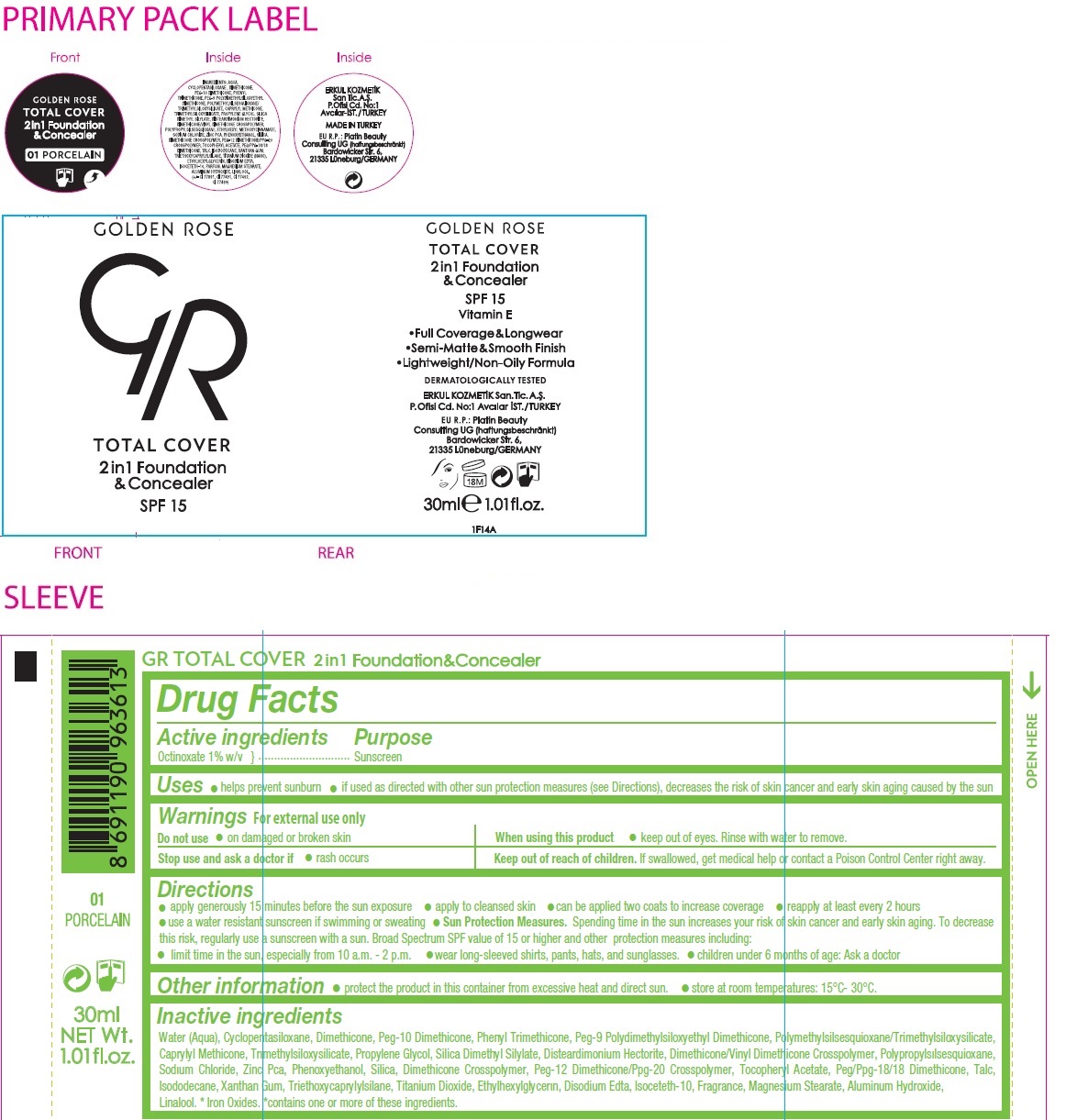 DRUG LABEL: GR TOTAL COVER 2 in 1 Foundation and Concealer SPF 15
NDC: 82715-106 | Form: LOTION
Manufacturer: ERKUL KOZMETIK SANAYI VE TICARET ANONIM SIRKETI
Category: otc | Type: HUMAN OTC DRUG LABEL
Date: 20250806

ACTIVE INGREDIENTS: OCTINOXATE 1 g/100 mL
INACTIVE INGREDIENTS: WATER; CYCLOMETHICONE 5; DIMETHICONE, UNSPECIFIED; PEG-10 DIMETHICONE (600 CST); PHENYL TRIMETHICONE; PEG-9 POLYDIMETHYLSILOXYETHYL DIMETHICONE; POLYMETHYLSILSESQUIOXANE/TRIMETHYLSILOXYSILICATE; CAPRYLYL TRISILOXANE; TRIMETHYLSILOXYSILICATE (M/Q 0.6-0.8); PROPYLENE GLYCOL; SILICA DIMETHYL SILYLATE; DISTEARDIMONIUM HECTORITE; DIMETHICONE/VINYL DIMETHICONE CROSSPOLYMER (SOFT PARTICLE); PROPYLSILSESQUIOXANE, HYDROGEN TERMINATED; SODIUM CHLORIDE; ZINC PIDOLATE; PHENOXYETHANOL; SILICON DIOXIDE; DIMETHICONE CROSSPOLYMER (450000 MPA.S); PEG-12 DIMETHICONE/PPG-20 CROSSPOLYMER; .ALPHA.-TOCOPHEROL ACETATE; PEG/PPG-18/18 DIMETHICONE; TALC; ISODODECANE; XANTHAN GUM; TRIETHOXYCAPRYLYLSILANE; TITANIUM DIOXIDE; ETHYLHEXYLGLYCERIN; EDETATE DISODIUM ANHYDROUS; ISOCETETH-10; MAGNESIUM STEARATE; ALUMINUM HYDROXIDE; LINALOOL, (+/-)-; FERRIC OXIDE RED; FERRIC OXIDE YELLOW; FERROSOFERRIC OXIDE

GR GOLDEN ROSE TOTAL COVER 2 in 1 Foundation & Concealer

Active ingredients

Octinoxate 1% w/v

Purpose

Sunscreen

Uses

• helps prevent sunburn • if used as directed with other sun protection measures (see Directions), decreases the risk of skin cancer and early skin aging caused by the sun

Warnings

For external use only

Do not use • on damaged or broken skin | When using this product • keep out of eyes. Rinse with water to remove.
Stop use and ask a doctor if • rash occurs

Keep out of reach of children. If swallowed, get medical help or contact a Poison Control Center right away.

Directions

• apply generously 15 minutes before the sun exposure • apply to cleansed skin • can be applied two coats to increase coverage • reapply at least every 2 hours • use a water resistant sunscreen if swimming or sweating • Sun Protection Measures. Spending time in the sun increases your risk of skin cancer and early skin aging. To decrease this risk, regularly use a sunscreen with a sun Broad Spectrum SPF value of 15 or higher and other protection measures including: • limit time in the sun, especially from 10 a.m. - 2 p.m. • wear long-sleeved shirts, pants, hats, and sunglasses. • children under 6 months of age: Ask a doctor

Other information

• protect the product in this container from excessive heat and direct sun. • store at room temperatures: 15°C- 30°C.

Inactive ingredients

Water (Aqua), Cyclopentasiloxane, Dimethicone, Peg-10 Dimethicone, Phenyl Trimethicone, Peg-9 Polydimethylsiloxyethyl Dimethicone, Polymethylsilsesquioxane/Trimethylsiloxysilicate, Caprylyl Methicone, Trımethylsiloxysilicate, Propylene Glycol, Silica Dimethyl Silylate, Disteardimonium Hectorite, Dimethicone/Vinyl Dimethicone Crosspolymer, Polypropylsılsesquioxane, Sodıum Chloride, Zinc Pca, Phenoxyethanol, Silica, Dimethicone Crosspolymer, Peg-12 Dimethicone/Ppg-20 Crosspolymer, Tocopheryl Acetate, Peg/Ppg-18/18 Dimethicone, Talc, Isododecane, Xanthan Gum, Triethoxycaprylylsilane, Titanium Dioxide, Ethylhexylglycerın, Disodium Edta, Isoceteth-10, Fragrance, Magnesium Stearate, Aluminum Hydroxide, Linalool. * Iron Oxides. *contains one or more of these ingredients.

SPF 15

Vitamin E

01 PORCELAIN

•Full Coverage & Longwear
•Semi-Matte & Smooth Finish
•Lightweight/Non-Oily Formula

DERMATOLOGICALLY TESTED

ERKUL KOZMETIK San. Tic. A.Ş.,
P.Ofisi Cd. No:1 Avcılar, IST./TURKEY

MADE IN TURKEY

EU R.P: Platin Beauty Consulting UG
(haftungsbeschränkt)
Bardowicker Str. 6,
21335 Lüneburg/GERMANY